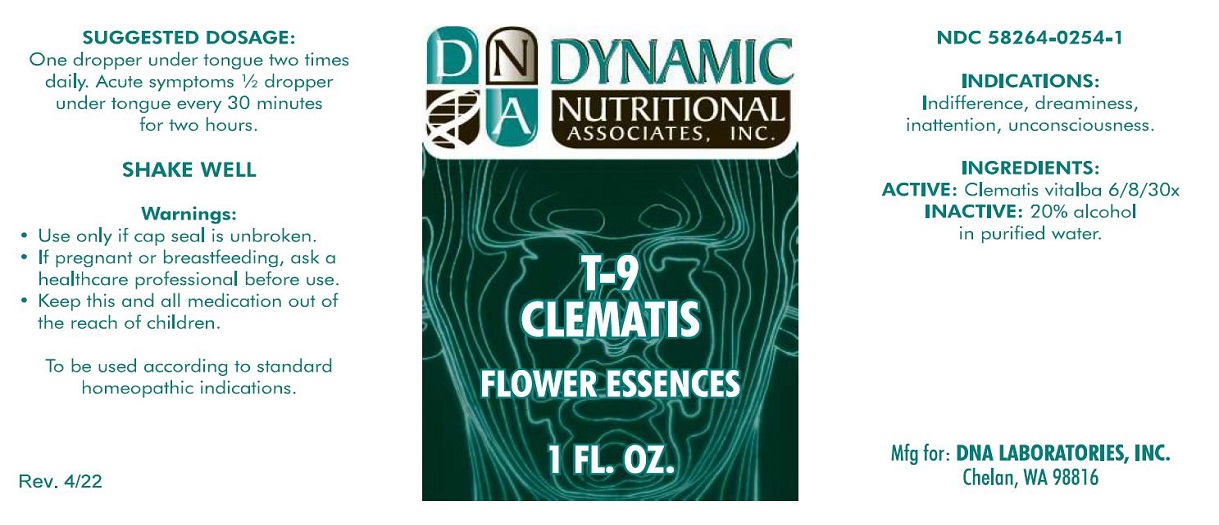 DRUG LABEL: T-9
NDC: 58264-0254 | Form: SOLUTION
Manufacturer: DNA Labs, Inc.
Category: homeopathic | Type: HUMAN OTC DRUG LABEL
Date: 20250109

ACTIVE INGREDIENTS: CLEMATIS VITALBA WHOLE 30 [hp_X]/1 mL
INACTIVE INGREDIENTS: ALCOHOL; WATER

T-9

NDC 58264-0254-1

INDICATIONS

PURPOSE

Indifference, dreaminess, inattention, unconsciousness.

INGREDIENTS

ACTIVE

Clematis vitalba 6/8/30x

INACTIVE

20% alcohol in purified water.

SUGGESTED DOSAGE

One dropper under tongue two times daily. Acute symptoms ½ dropper under tongue every 30 minutes for two hours.

STORAGE AND HANDLING

SHAKE WELL

Warnings

WHEN USING

- Use only if cap seal is unbroken.

PREGNANCY OR BREAST FEEDING

- If pregnant or breastfeeding, ask a healthcare professional before use.

KEEP OUT OF REACH OF CHILDREN

- Keep this and all medication out of the reach of children.

To be used according to standard homeopathic indications.

PRINCIPAL DISPLAY PANEL - 1 FL. OZ. Bottle Label

DYNAMIC
NUTRITIONAL
ASSOCIATES, INC.

T-9
CLEMATIS

FLOWER ESSENCES

1 FL. OZ.